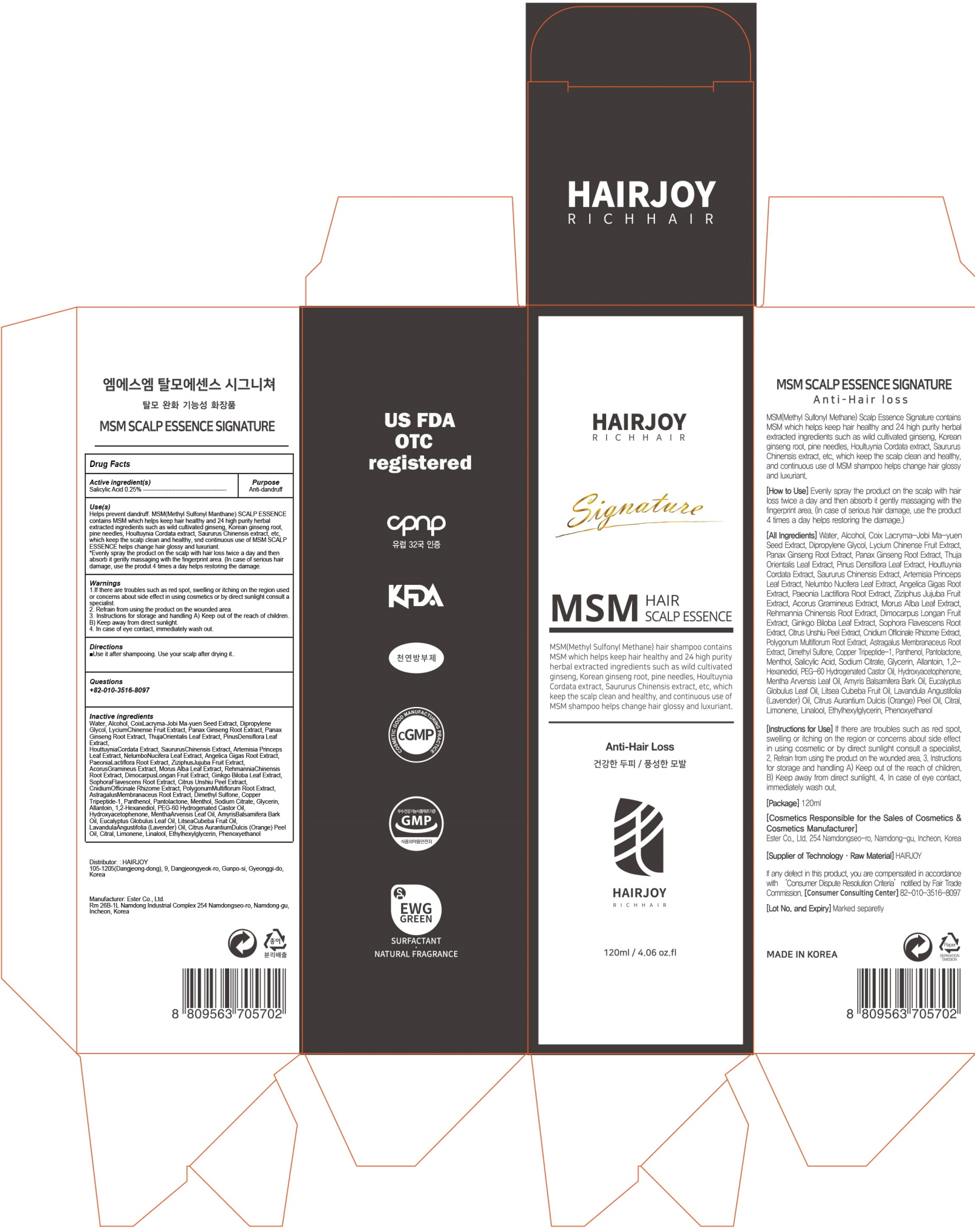 DRUG LABEL: MSM SCALP ESSENCE SIGNATURE
NDC: 69384-070 | Form: LIQUID
Manufacturer: HAIRJOY
Category: otc | Type: HUMAN OTC DRUG LABEL
Date: 20200825

ACTIVE INGREDIENTS: Salicylic Acid 0.3 g/120 mL
INACTIVE INGREDIENTS: Water; Alcohol

ACTIVE INGREDIENT

Salicylic Acid 0.25%

INACTIVE INGREDIENTS

Water, Alcohol, CoixLacryma-Jobi Ma-yuen Seed Extract, Dipropylene Glycol, LyciumChinense Fruit Extract, Panax Ginseng Root Extract, Panax Ginseng Root Extract, ThujaOrientalis Leaf Extract, PinusDensiflora Leaf Extract, HouttuyniaCordata Extract, SaururusChinensis Extract, Artemisia Princeps Leaf Extract, NelumboNucifera Leaf Extract, Angelica Gigas Root Extract, PaeoniaLactiflora Root Extract, ZiziphusJujuba Fruit Extract, AcorusGramineus Extract, Morus Alba Leaf Extract, RehmanniaChinensis Root Extract, DimocarpusLongan Fruit Extract, Ginkgo Biloba Leaf Extract, SophoraFlavescens Root Extract, Citrus Unshiu Peel Extract, CnidiumOfficinale Rhizome Extract, PolygonumMultiflorum Root Extract, AstragalusMembranaceus Root Extract, Dimethyl Sulfone, Copper Tripeptide-1, Panthenol, Pantolactone, Menthol, Sodium Citrate, Glycerin, Allantoin, 1,2-Hexanediol, PEG-60 Hydrogenated Castor Oil, Hydroxyacetophenone, MenthaArvensis Leaf Oil, AmyrisBalsamifera Bark Oil, Eucalyptus Globulus Leaf Oil, LitseaCubeba Fruit Oil, LavandulaAngustifolia (Lavender) Oil, Citrus AurantiumDulcis (Orange) Peel Oil, Citral, Limonene, Linalool, Ethylhexylglycerin, Phenoxyethanol

PURPOSE

Anti-dandruff

WARNINGS

1.If there are troubles such as red spot, swelling or itching on the region used or concerns about side effect in using cosmetics or by direct sunlight consult a specialist.
2. Refrain from using the product on the wounded area.
3. Instructions for storage and handling A) Keep out of the reach of children. B) Keep away from direct sunlight.
4. In case of eye contact, immediately wash out.

KEEP OUT OF REACH OF CHILDREN

Uses

Helps prevent dandruff. MSM(Methyl Sulfonyl Manthane) SCALP ESSENCE contains MSM which helps keep hair healthy and 24 high purity herbal extracted ingredients such as wild cultivated ginseng, Korean ginseng root, pine needles, Houltuynia Cordata extract, Saururus Chinensis extract, etc, which keep the scalp clean and healthy, snd continuous use of MSM SCALP ESSENCE helps change hair glossy and luxuriant.
*Evenly spray the product on the scalp with hair loss twice a day and then absorb it gently massaging with the fingerprint area. (In case of serious hair damage, use the produt 4 times a day helps restoring the damage.

Directions

■Use it after shampooing. Use your scalp after drying it.

QUESTIONS

+82-010-3516-8097